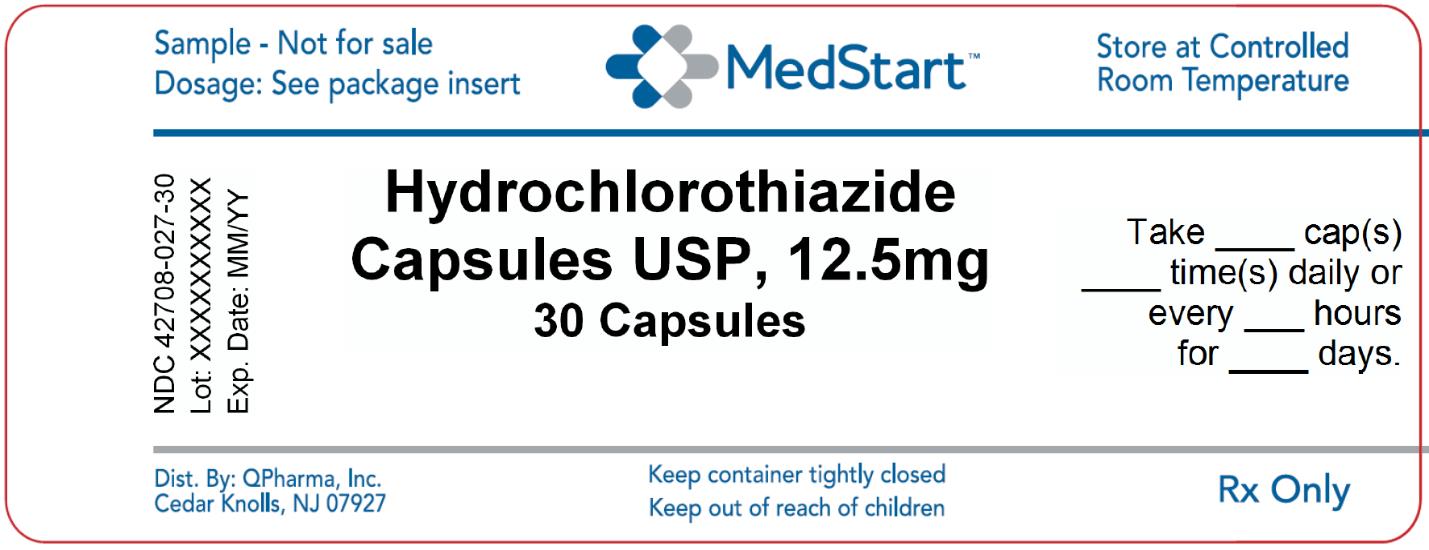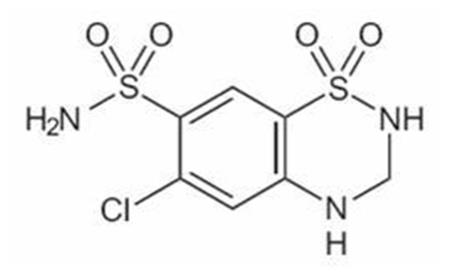 DRUG LABEL: Hydrochlorothiazide
NDC: 42708-027 | Form: CAPSULE, GELATIN COATED
Manufacturer: QPharma, Inc.
Category: prescription | Type: HUMAN PRESCRIPTION DRUG LABEL
Date: 20251205

ACTIVE INGREDIENTS: HYDROCHLOROTHIAZIDE 12.5 mg/1 1
INACTIVE INGREDIENTS: SILICON DIOXIDE; STARCH, CORN; D&C RED NO. 28; D&C YELLOW NO. 10; FD&C BLUE NO. 1; GELATIN; LACTOSE MONOHYDRATE; MAGNESIUM STEARATE; TITANIUM DIOXIDE; FERROSOFERRIC OXIDE; FD&C BLUE NO. 2; FD&C RED NO. 40

Hydrochlorothiazide Capsules, USP

Rx only

DESCRIPTION

Hydrochlorothiazide Capsules, USP, 12.5 mg is the 3,4-dihydro derivative of chlorothiazide. Its chemical name is 6-chloro-3,4-dihydro-2 H-1,2,4-benzothiadiazine-7-sulfonamide 1,1-dioxide. Its empirical formula is C7H8ClN3O4S2; its molecular weight is 297.74; and its structural formula is:

It is a white, or practically white, crystalline powder which is slightly soluble in water, but freely soluble in sodium hydroxide solution.

Hydrochlorothiazide is supplied as 12.5 mg capsules for oral use.

Inactive ingredients: colloidal silicon dioxide, corn starch, lactose monohydrate, magnesium stearate. Gelatin capsules contain D&C Red No. 28, D&C Yellow No. 10, FD&C Blue No. 1, gelatin, titanium dioxide. The capsules are printed with edible ink containing black iron oxide, D&C Yellow No. 10, FD&C Blue No. 1, FD&C Blue No. 2, FD&C Red No. 40.

CLINICAL PHARMACOLOGY

Hydrochlorothiazide blocks the reabsorption of sodium and chloride ions, and it thereby increases the quantity of sodium traversing the distal tubule and the volume of water excreted. A portion of the additional sodium presented to the distal tubule is exchanged there for potassium and hydrogen ions. With continued use of hydrochlorothiazide and depletion of sodium, compensatory mechanisms tend to increase this exchange and may produce excessive loss of potassium, hydrogen and chloride ions. Hydrochlorothiazide also decreases the excretion of calcium and uric acid, may increase the excretion of iodide and may reduce glomerular filtration rate. Metabolic toxicities associated with excessive electrolyte changes caused by hydrochlorothiazide have been shown to be dose-related.

Pharmacokinetics and Metabolism:

Hydrochlorothiazide is well absorbed (65% to 75%) following oral administration. Absorption of hydrochlorothiazide is reduced in patients with congestive heart failure.

Peak plasma concentrations are observed within 1 to 5 hours of dosing and range from 70 to 490 ng/mL following oral doses of 12.5 to 100 mg. Plasma concentrations are linearly related to the administered dose. Concentrations of hydrochlorothiazide are 1.6 to 1.8 times higher in whole blood than in plasma. Binding to serum proteins has been reported to be approximately 40% to 68%. The plasma elimination half-life has been reported to be 6 to 15 hours. Hydrochlorothiazide is eliminated primarily by renal pathways. Following oral doses of 12.5 to 100 mg, 55% to 77% of the administered dose appears in urine and greater than 95% of the absorbed dose is excreted in urine as unchanged drug. In patients with renal disease, plasma concentrations of hydrochlorothiazide are increased and the elimination half-life is prolonged.

When hydrochlorothiazide is administered with food, its bioavailability is reduced by 10%, the maximum plasma concentration is reduced by 20%, and the time to maximum concentration increases from 1.6 to 2.9 hours.

Pharmacodynamics:

Acute antihypertensive effects of thiazides are thought to result from a reduction in blood volume and cardiac output, secondary to a natriuretic effect, although a direct vasodilatory mechanism has also been proposed. With chronic administration, plasma volume returns toward normal, but peripheral vascular resistance is decreased. The exact mechanism of the antihypertensive effect of hydrochlorothiazide is not known.

Thiazides do not affect normal blood pressure. Onset of action occurs within 2 hours of dosing, peak effect is observed at about 4 hours, and activity persists for up to 24 hours.

Clinical Studies:

In an 87 patient 4-week double-blind, placebo controlled, parallel group trial, patients who received hydrochlorothiazide had reductions in seated systolic and diastolic blood pressure that were significantly greater than those seen in patients who received placebo. In published placebo-controlled trials comparing 12.5 mg of hydrochlorothiazide to 25 mg, the 12.5 mg dose preserved most of the placebo-corrected blood pressure reduction seen with 25 mg.

INDICATIONS AND USAGE

Hydrochlorothiazide is indicated in the management of hypertension either as the sole therapeutic agent, or in combination with other antihypertensives. Unlike potassium sparing combination diuretic products, hydrochlorothiazide may be used in those patients in whom the development of hyperkalemia cannot be risked, including patients taking ACE inhibitors.

Usage in Pregnancy:The routine use of diuretics in an otherwise healthy woman is inappropriate and exposes mother and fetus to unnecessary hazard. Diuretics do not prevent development of toxemia of pregnancy, and there is no satisfactory evidence that they are useful in the treatment of developed toxemia.

Edema during pregnancy may arise from pathological causes or from the physiologic and mechanical consequences of pregnancy. Diuretics are indicated in pregnancy when edema is due to pathologic causes, just as they are in the absence of pregnancy. Dependent edema in pregnancy resulting from restriction of venous return by the expanded uterus is properly treated through elevation of the lower extremities and use of support hose; use of diuretics to lower intravascular volume in this case is illogical and unnecessary. There is hypervolemia during normal pregnancy which is harmful to neither the fetus nor the mother (in the absence of cardiovascular disease), but which is associated with edema, including generalized edema in the majority of pregnant women. If this edema produces discomfort, increased recumbency will often provide relief. In rare instances this edema may cause extreme discomfort which is not relieved by rest. In these cases a short course of diuretics may provide relief and may be appropriate.

CONTRAINDICATIONS

Hydrochlorothiazide is contraindicated in patients with anuria. Hypersensitivity to this product or other sulfonamide derived drugs is also contraindicated.

WARNINGS

Acute Myopia and Secondary Angle-Closure Glaucoma:Hydrochlorothiazide, a sulfonamide, can cause an idiosyncratic reaction, resulting in acute transient myopia and acute angle-closure glaucoma. Symptoms include acute onset of decreased visual acuity or ocular pain and typically occur within hours to weeks of drug initiation. Untreated acute angle-closure glaucoma can lead to permanent vision loss. The primary treatment is to discontinue hydrochlorothiazide as rapidly as possible. Prompt medical or surgical treatments may need to be considered if the intraocular pressure remains uncontrolled. Risk factors for developing acute angle-closure glaucoma may include a history of sulfonamide or penicillin allergy.

Diabetes and Hypoglycemia:Latent diabetes mellitus may become manifest and diabetic patients given thiazides may require adjustment of their insulin dose.

Renal Disease:Cumulative effects of the thiazides may develop in patients with impaired renal function. In such patients, thiazides may precipitate azotemia.

PRECAUTIONS

Electrolyte and Fluid Balance Status:In published studies, clinically significant hypokalemia has been consistently less common in patients who received 12.5 mg of hydrochlorothiazide than in patients who received higher doses. Nevertheless, periodic determination of serum electrolytes should be performed in patients who may be at risk for the development of hypokalemia. Patients should be observed for signs of fluid or electrolyte disturbances, i.e., hyponatremia, hypochloremic alkalosis, and hypokalemia and hypomagnesemia.

Warning signs or symptoms of fluid and electrolyte imbalance include dryness of mouth, thirst, weakness, lethargy, drowsiness, restlessness, muscle pains or cramps, muscular fatigue, hypotension, oliguria, tachycardia, and gastrointestinal disturbances such as nausea and vomiting.

Hypokalemia may develop, especially with brisk diuresis when severe cirrhosis is present, during concomitant use of corticosteroid or adrenocorticotropic hormone (ACTH) or after prolonged therapy. Interference with adequate oral electrolyte intake will also contribute to hypokalemia. Hypokalemia and hypomagnesemia can provoke ventricular arrhythmias or sensitize or exaggerate the response of the heart to the toxic effects of digitalis. Hypokalemia may be avoided or treated by potassium supplementation or increased intake of potassium rich foods.

Dilutional hyponatremia is life-threatening and may occur in edematous patients in hot weather; appropriate therapy is water restriction rather than salt administration, except in rare instances when the hyponatremia is life-threatening. In actual salt depletion, appropriate replacement is the therapy of choice.

Hyperuricemia:Hyperuricemia or acute gout may be precipitated in certain patients receiving thiazide diuretics.

Impaired Hepatic Function:Thiazides should be used with caution in patients with impaired hepatic function. They can precipitate hepatic coma in patients with severe liver disease.

Parathyroid Disease:Calcium excretion is decreased by thiazides, and pathologic changes in the parathyroid glands, with hypercalcemia and hypophosphatemia, have been observed in a few patients on prolonged thiazide therapy.

Information for Patients:

Non-melanoma Skin Cancer:Instruct patients taking hydrochlorothiazide to protect skin from the sun and undergo regular skin cancer screening.

Drug Interactions:

When given concurrently the following drugs may interact with thiazide diuretics:

Alcohol, barbiturates, or narcotics- potentiation of orthostatic hypotension may occur.

Antidiabetic drugs- (oral agents and insulin) dosage adjustment of the antidiabetic drug may be required.

Other antihypertensive drugs- additive effect or potentiation.

Cholestyramine and colestipol resins- Cholestyramine and colestipol resins bind the hydrochlorothiazide and reduce its absorption from the gastrointestinal tract by up to 85 and 43 percent, respectively.

Corticosteroid, ACTH– intensified electrolyte depletion, particularly hypokalemia.

Pressor amines (e.g., norepinephrine)- possible decreased response to pressor amines but not sufficient to preclude their use.

Skeletal muscle relaxants, nondepolarizing (e.g., tubocurarine)- possible increased responsiveness to the muscle relaxant.

Lithium- generally should not be given with diuretics. Diuretic agents reduce the renal clearance of lithium and greatly increase the risk of lithium toxicity. Refer to the package insert for lithium preparations before use of such preparations with hydrochlorothiazide.

Non-steroidal anti-inflammatory drugs- In some patients, the administration of a non-steroidal anti-inflammatory agent can reduce the diuretic, natriuretic, and antihypertensive effects of loop, potassium-sparing and thiazide diuretics. When hydrochlorothiazide and non-steroidal anti-inflammatory agents are used concomitantly, the patients should be observed closely to determine if the desired effect of the diuretic is obtained.

Drug/Laboratory Test Interactions- Thiazides should be discontinued before carrying out tests for parathyroid function (see PRECAUTIONS, General).

Carcinogenesis, Mutagenesis, Impairment of Fertility:Two-year feeding studies in mice and rats conducted under the auspices of the National Toxicology Program (NTP) uncovered no evidence of a carcinogenic potential of hydrochlorothiazide in female mice (at doses of up to approximately 600 mg/kg/day) or in male and female rats (at doses of approximately 100 mg/kg/day). The NTP, however, found equivocal evidence for hepatocarcinogenicity in male mice. Hydrochlorothiazide was not genotoxic in vitroin the Ames mutagenicity assay of Salmonella typhimuriumstrains TA 98, TA 100, TA 1535, TA 1537, and TA 1538 and in the Chinese Hamster Ovary (CHO) test for chromosomal aberrations, or in vivoin assays using mouse germinal cell chromosomes, Chinese hamster bone marrow chromosomes, and the Drosophilasex-linked recessive lethal trait gene. Positive test results were obtained only in the in vitroCHO Sister Chromatid Exchange (clastogenicity) and in the Mouse Lymphoma Cell (mutagenicity) assays, using concentrations of hydrochlorothiazide from 43 to 1,300 mcg/mL, and in the Aspergillus nidulansnon-disjunction assay at an unspecified concentration.

Hydrochlorothiazide had no adverse effects on the fertility of mice and rats of either sex in studies wherein these species were exposed, via their diet, to doses of up to 100 and 4 mg/kg, respectively, prior to conception and throughout gestation.

Pregnancy:

Teratogenic Effects:

Studies in which hydrochlorothiazide was orally administered to pregnant mice and rats during their respective periods of major organogenesis at doses up to 3,000 and 1,000 mg hydrochlorothiazide/kg, respectively, provided no evidence of harm to the fetus.

There are, however, no adequate and well-controlled studies in pregnant women. Because animal reproduction studies are not always predictive of human response, this drug should be used during pregnancy only if clearly needed.

Nonteratogenic Effects:

Thiazides cross the placental barrier and appear in cord blood. There is a risk of fetal or neonatal jaundice, thrombocytopenia, and possibly other adverse reactions that have occurred in adults.

Nursing Mothers:

Thiazides are excreted in breast milk. Because of the potential for serious adverse reactions in nursing infants, a decision should be made whether to discontinue nursing or to discontinue hydrochlorothiazide, taking into account the importance of the drug to the mother.

Pediatric Use:

Safety and effectiveness in pediatric patients have not been established.

Elderly Use:

A greater blood pressure reduction and an increase in side effects may be observed in the elderly (i.e., > 65 years) with hydrochlorothiazide. Starting treatment with the lowest available dose of hydrochlorothiazide (12.5 mg) is therefore recommended. If further titration is required, 12.5 mg increments should be utilized.

ADVERSE REACTIONS

The adverse reactions associated with hydrochlorothiazide have been shown to be dose related. In controlled clinical trials, the adverse events reported with doses of 12.5 mg hydrochlorothiazide once daily were comparable to placebo. The following adverse reactions have been reported for doses of hydrochlorothiazide 25 mg and greater and, within each category, are listed in the order of decreasing severity.

Body as a whole:Weakness.

Cardiovascular:Hypotension including orthostatic hypotension (may be aggravated by alcohol, barbiturates, narcotics or antihypertensive drugs).

Digestive:Pancreatitis, jaundice (intrahepatic cholestatic jaundice), diarrhea, vomiting, sialadenitis, cramping, constipation, gastric irritation, nausea, anorexia.

Hematologic:Aplastic anemia, agranulocytosis, leukopenia, hemolytic anemia, thrombocytopenia.

Hypersensitivity:Anaphylactic reactions, necrotizing angiitis (vasculitis and cutaneous vasculitis), respiratory distress including pneumonitis and pulmonary edema, photosensitivity, fever, urticaria, rash, purpura.

Metabolic:Electrolyte imbalance (see PRECAUTIONS), hyperglycemia, glycosuria, hyperuricemia.

Musculoskeletal:Muscle spasm.

Nervous System/Psychiatric:Vertigo, paresthesia, dizziness, headache, restlessness.

Renal:Renal failure, renal dysfunction, interstitial nephritis (see WARNINGS).

Skin:Erythema multiforme including Stevens-Johnson syndrome, exfoliative dermatitis including toxic epidermal necrolysis, alopecia.

Special Senses:Transient blurred vision, xanthopsia.

Urogenital:Impotence.

Whenever adverse reactions are moderate or severe, thiazide dosage should be reduced or therapy withdrawn.

Postmarketing Experience:

The following adverse reaction has been identified during post-approval use of hydrochlorothiazide. Because the reaction is reported voluntarily from a population of uncertain size, it is not possible to reliably estimate the frequency or establish a causal relationship to drug exposure.

Non-melanoma Skin Cancer: Hydrochlorothiazide is associated with an increased risk of non-melanoma skin cancer. In a study conducted in the Sentinel System, increased risk was predominantly for squamous cell carcinoma (SCC) and in white patients taking large cumulative doses. The increased risk for SCC in the overall population was approximately 1 additional case per 16,000 patients per year, and for white patients taking a cumulative dose of ≥50,000 mg the risk increase was approximately 1 additional SCC case for every 6,700 patients per year.

OVERDOSAGE

The most common signs and symptoms observed are those caused by electrolyte depletion (hypokalemia, hypochloremia, hyponatremia) and dehydration resulting from excessive diuresis. If digitalis has also been administered, hypokalemia may accentuate cardiac arrhythmias.

In the event of overdosage, symptomatic and supportive measures should be employed. Emesis should be induced or gastric lavage performed. Correct dehydration, electrolyte imbalance, hepatic coma and hypotension by established procedures. If required, give oxygen or artificial respiration for respiratory impairment. The degree to which hydrochlorothiazide is removed by hemodialysis has not been established.

The oral LD50of hydrochlorothiazide is greater than 10 gm/kg in the mouse and rat.

DOSAGE AND ADMINISTRATION

For Control of Hypertension:The adult initial dose of hydrochlorothiazide is one capsule given once daily whether given alone or in combination with other antihypertensives. Total daily doses greater than 50 mg are not recommended.

HOW SUPPLIED

Hydrochlorothiazide Capsules, USP are #4 Teal Opaque/White Opaque two piece hard gelatin capsules imprinted with WATSON 347 and 12.5 mg in black ink. They are supplied in bottles of 30 (NDC 42708-027-30) are supplied with child resistant closures.

Dispense in a tight, light-resistant container as defined in the USP.

Keep out of reach of children.

Store at 20°C to 25°C (68°F to 77°F). [See USP controlled room temperature.] Protect from light, moisture, freezing, -20°C (-4°F). Keep container tightly closed.

Manufactured for:
Teva Pharmaceuticals
Parsippany, NJ 07054

Rev. 12/2023

Principal Display Panel

NDC: 42708-027-30